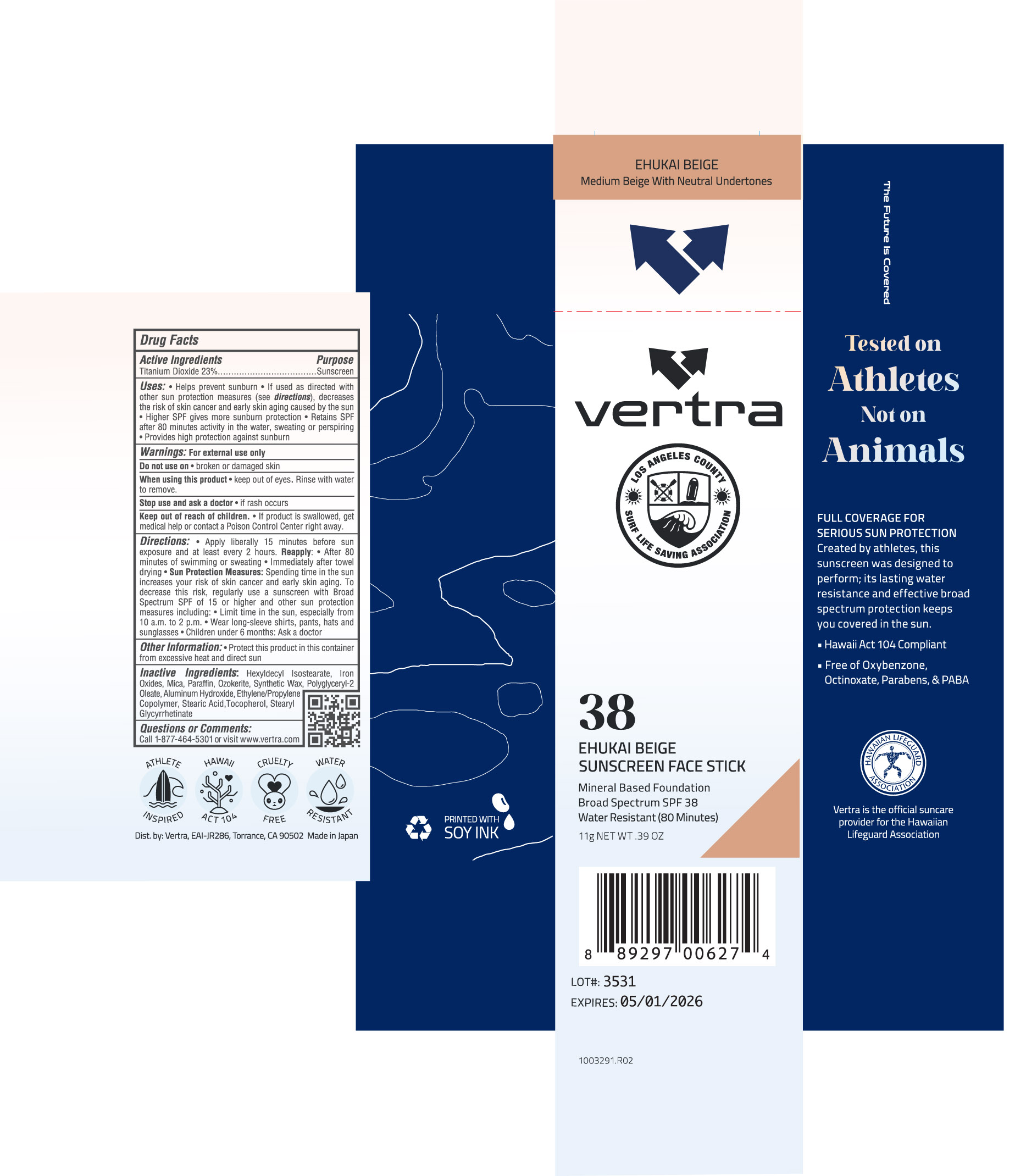 DRUG LABEL: Vertra Ehukai Beige Sunscreen Face Stick Broad Spectrum SPF 38
NDC: 71014-040 | Form: STICK
Manufacturer: Eai-jr 286, Inc
Category: otc | Type: HUMAN OTC DRUG LABEL
Date: 20250313

ACTIVE INGREDIENTS: TITANIUM DIOXIDE 23 g/100 g
INACTIVE INGREDIENTS: PARAFFIN; CERESIN; MICA; STEARYL GLYCYRRHETINATE; HEXYLDECYL ISOSTEARATE; IRON OXIDES; POLYGLYCERYL-2 OLEATE; SYNTHETIC WAX (540 MW); STEARIC ACID; TOCOPHEROL; ALUMINUM HYDROXIDE

Vertra Ehukai Beige Sunscreen Face Stick SPF 38 LA Lifeguard

Active ingredients Purpose

Titanium Dioxide 23% Sunscreen

PURPOSE

- Uses: helps prevent sunnurn
- If used as directed with other skin protection measures (see directions), decreases the risk of skin cancer and early skin aging by the sun.
- Higher SPF gives more sunburn protection
- Retains SPF after 80 minutes activity in the water, sweating or perspiring
- Provides high protection against sunburn

Keep out of reach of children. If product is swallowed, get medical help or contact a Poison Control Center right away.

- Stop use and ask a doctor if rash occurs.

Warnings: For external use only

- Do not use on broken or damaged skin
- When using this product Keep out of eyes. Rinse with water to remove.

Directions

- Apply liberally and evenly 15 minutes before sun exposure and at least every 2 hours.

Reapply:

- After 80 minutes of swimming or sweating
- Immediately after towel drying

Sun Protection Measures. spending time in the sun increases your risk of skin cancer and early skin aging. To decrease this risk, regularly use a sunscreen with a Broad Spectrum value 15 or higher and other sun protection measures including:

- Limit time in the sun, especially from 10 a.m.-2p.m.
- Wear long-sleeve shirts, pants, hats and sunglasses
- Children under 6 months of age: ask a doctor

INACTIVE INGREDIENT

Inactive Ingredients: Hexyldecyl Isostearate, Iron Oxides, Mica, Paraffin, Ozokerite, Synthetic Wax, Polyglyceryl-2 Oleate, Aluminum Hydroxide, Ethylene/Propylene Copolymer, Stearic Acid, Tocopherol, Stearyl Glycyrrhetinate.

PACKAGE LABEL

vertra

38 Ehukai Beige

Sunscreen Face Stick

Mineral Based Foundation

Broad Spectrum SPF 38

Water resistant (80 minutes)

11g NET WT .39 OZ